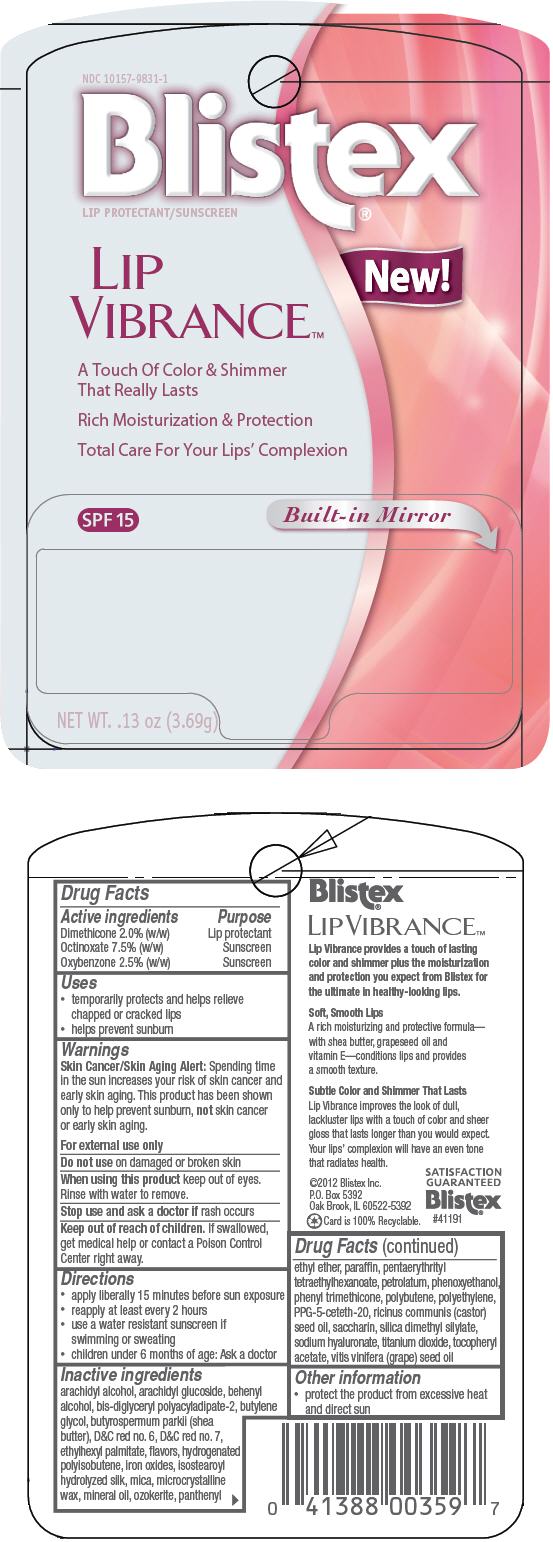 DRUG LABEL: Blistex 
NDC: 10157-9831 | Form: STICK
Manufacturer: Blistex Inc.
Category: otc | Type: HUMAN OTC DRUG LABEL
Date: 20130326

ACTIVE INGREDIENTS: Octinoxate 7.5 g/100 g; Oxybenzone 2.5 g/100 g; Dimethicone 2 g/100 g
INACTIVE INGREDIENTS: arachidyl alcohol; arachidyl glucoside; docosanol; butylene glycol; shea butter; D&C red no. 6; D&C red no. 7; ethylhexyl palmitate; mica; microcrystalline wax; mineral oil; panthenyl ethyl ether; paraffin; pentaerythrityl tetraethylhexanoate; petrolatum; phenoxyethanol; phenyl trimethicone; high density polyethylene; PPG-5-ceteth-20; castor oil; saccharin; silica dimethyl silylate; hyaluronate sodium; titanium dioxide; .alpha.-tocopherol acetate; grape seed oil; ferric oxide red; ceresin; sandalwood

Blistex®
Lip Vibrance™

Drug Facts

ACTIVE INGREDIENT

Active ingredients | Purpose
Dimethicone 2.0% (w/w) | Lip protectant
Octinoxate 7.5% (w/w) | Sunscreen
Oxybenzone 2.5% (w/w) | Sunscreen

Uses

- temporarily protects and helps relieve chapped or cracked lips
- helps prevent sunburn

Warnings

Skin Cancer/Skin Aging Alert

Spending time in the sun increases your risk of skin cancer and early skin aging. This product has been shown only to help prevent sunburn, not skin cancer or early skin aging.

For external use only

Do not use on damaged or broken skin

When using this product keep out of eyes. Rinse with water to remove.

Stop use and ask a doctor if rash occurs

Keep out of reach of children. If swallowed, get medical help or contact a Poison Control Center right away.

Directions

- apply liberally 15 minutes before sun exposure
- reapply at least every 2 hours
- use a water resistant sunscreen if swimming or sweating
- children under 6 months of age: Ask a doctor

Inactive ingredients

arachidyl alcohol, arachidyl glucoside, behenyl alcohol, bis-diglyceryl polyacyladipate-2, butylene glycol, butyrospermum parkii (shea butter), D&C red no. 6, D&C red no. 7, ethylhexyl palmitate, flavors, hydrogenated polyisobutene, iron oxides, isostearoyl hydrolyzed silk, mica, microcrystalline wax, mineral oil, ozokerite, panthenyl ethyl ether, paraffin, pentaerythrityl tetraethylhexanoate, petrolatum, phenoxyethanol, phenyl trimethicone, polybutene, polyethylene, PPG-5-ceteth-20, ricinus communis (castor) seed oil, saccharin, silica dimethyl silylate, sodium hyaluronate, titanium dioxide, tocopheryl acetate, vitis vinifera (grape) seed oil

Other information

- protect the product from excessive heat and direct sun

PRINCIPAL DISPLAY PANEL - 3.69g Container Blister Pack

NDC 10157-9831-1
Blistex®
LIP PROTECTANT/SUNSCREEN

LIP
VIBRANCE™

New!

A Touch Of Color & Shimmer
That Really Lasts

Rich Moisturization & Protection

Total Care For Your Lips' Complexion

SPF 15

Built-in Mirror

NET WT. .13 oz (3.69g)